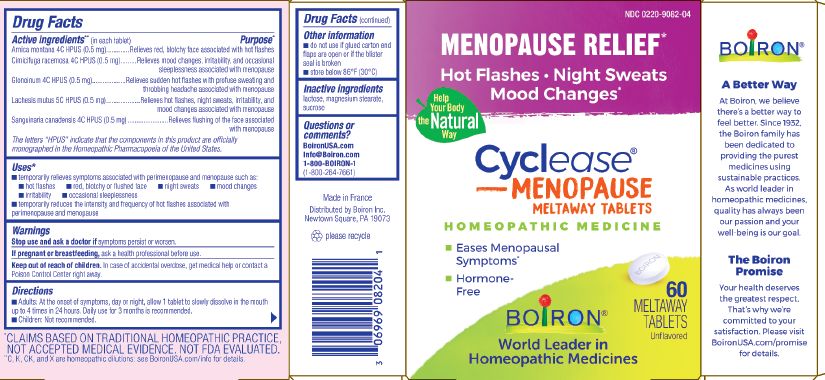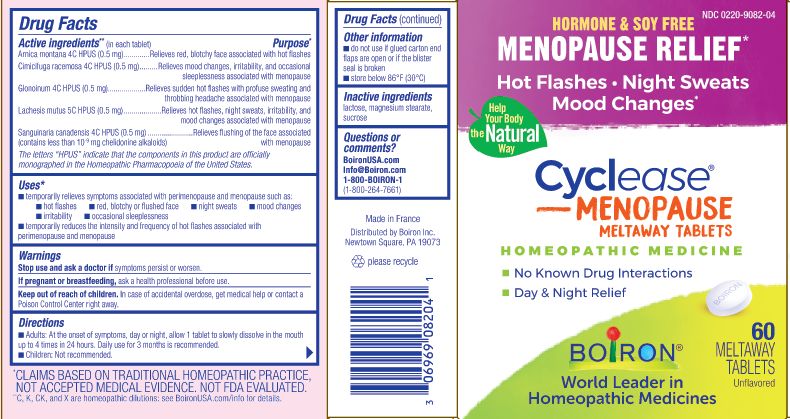 DRUG LABEL: Cyclease Menopause
NDC: 0220-9082 | Form: TABLET
Manufacturer: Boiron
Category: homeopathic | Type: HUMAN OTC DRUG LABEL
Date: 20230816

ACTIVE INGREDIENTS: NITROGLYCERIN 4 [hp_C]/1 1; BLACK COHOSH 4 [hp_C]/1 1; LACHESIS MUTA VENOM 5 [hp_C]/1 1; SANGUINARIA CANADENSIS ROOT 4 [hp_C]/1 1; ARNICA MONTANA WHOLE 4 [hp_C]/1 1
INACTIVE INGREDIENTS: LACTOSE, UNSPECIFIED FORM; MAGNESIUM STEARATE; SUCROSE

Cyclease Menopause

Active ingredients** (in each tablet)

Arnica montana 4C HPUS (0.5mg)

Cimicifuga racemosa 4C HPUS (0.5mg)

Glonoinum 4C HPUS (0.5mg)

Lachesis mutus 5C HPUS (0.5mg)

Sanguinaria canadensis 4C HPUS (0.5mg) (contains less than 10^-9 mg chelidonine alkaloids)

The letters "HPUS" indicate that the components in this product are officially monographed in the Homeopathic Pharmacopoeia of the United States.

Purpose*

Arnica montana 4C HPUS (0.5mg) ... Relieves red, blotchy face associated with hot flashes

Cimicifuga racemosa 4C HPUS (0.5mg) ... Relieves mood changes, irritability, and occasional sleeplessness associated with menopause

Glonoinum 4C HPUS (0.5mg) ... Relieves sudden hot flashes with profuse sweating and throbbing headache associated with menopause

Lachesis mutus 5C HPUS (0.5mg) ... Relieves hot flashes, night sweats, irritability, and mood changes associated with menopause

Sanguinaria canadensis 4C HPUS (0.5mg) ... Relieves flushing of the face associated with menopause

Uses*

temporarily relieves symptoms associated with perimenopause and menopause such as:

- hot flashes
- red, blotchy or flushed face
- night sweats
- mood changes
- irritability
- occasional sleeplessness

temporarily reduces the intensity and frequency of hot flashes associated with perimenopause and menopause

Warnings

Stop use and ask a doctor if symptoms persist or worsen.

PREGNANCY OR BREAST FEEDING

If pregnant or breastfeeding, ask a health professional before use.

Keep out of reach of children. In case of accidental overdose, get medical help or contact a Poison Control Center right away.

Directions

Adults: At the onset of symptoms, day or night, allow 1 tablet to slowly dissolve in the mouth up to 4 times in 24 hours. Daily use for 3 months is recommended.

Children: Not recommended.

Do not use if glued carton end flaps are open or if the blister seal is broken.

Store below 86° F (30° C)

60 meltaway tablets unflavored

Hormone & Soy Relief

Menopause relief*

Hot Flashes Night Sweats Mood Changes*

No Known Drug Interactions

Day & Night Relief

*CLAIMS BASED ON TRADITIONAL HOMEOPATHIC PRACTICE NOT ACCEPTED MEDICAL EVIDENCE. NOT FDA EVALUATED.
**C,K,CK, and X are homeopathic dilutions: see BoironUSA.com/info for details.

INACTIVE INGREDIENT

lactose, magnesium stearate, sucrose

Questions or comments?

1-800-BOIRON-1 (1-800-264-7661),
BoironUSA.com Info@boiron.com
Distributed by Boiron, Inc. Newtown Square, PA 19073

Made in France